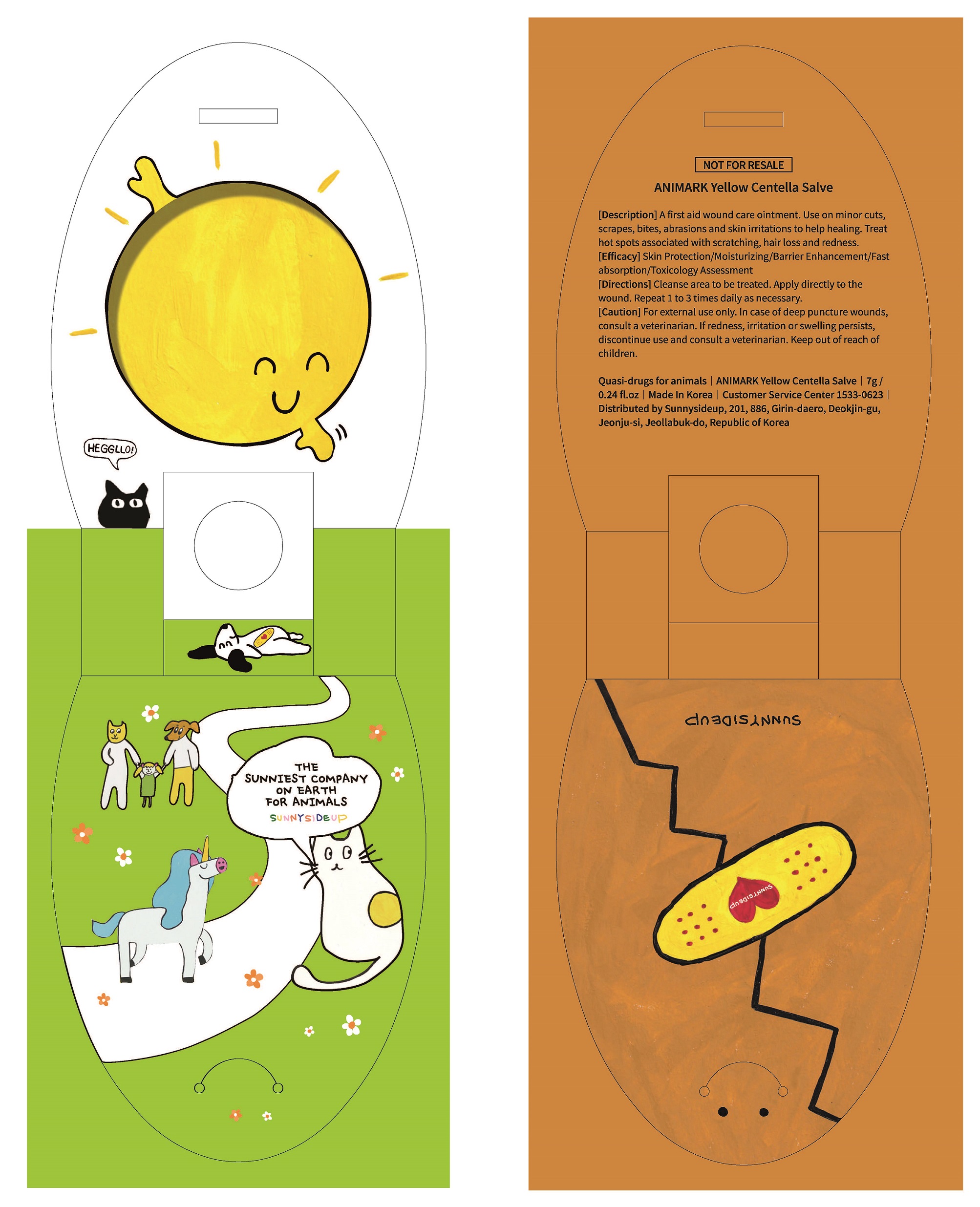 DRUG LABEL: ANIMARK YELLOW CENTELLASALVE
NDC: 74339-0001 | Form: SALVE
Manufacturer: PL COSMETIC
Category: animal | Type: OTC ANIMAL DRUG LABEL
Date: 20220806

ACTIVE INGREDIENTS: CETOSTEARYL ALCOHOL 0.06 g/1 g
INACTIVE INGREDIENTS: WATER; GLYCERIN

ACTIVE INGREDIENT

Cetearyl Alcohol

INACTIVE INGREDIENT

Butyrospermum Parkii (Shea) Butter
Arachidyl Alcohol, Behenyl Alcohol, Arachidyl Glucoside
Glycerin
Olea Europaea (Olive) Fruit Oil
Vitis Vinifera (Grape) Seed Oil
Glyceryl Stearate
Asiaticoside, Madecassoside, Dextrin
Sea Water, Butylene Glycol
Lysozyme
1,2-Hexanediol
Persea Gratissima (Avocado) Oil
Calendula Officinalis Flower Extract
Phellodendron Amurense Bark Extract
Sorbitan Stearate
Sorbitan Sesquioleate
Sodium Hyaluronate
Xanthan Gum
Dipotassium Glycyrrhizate
Tocopherol
Disodium EDTA
Arginine
Hydroxyacetophenone

PURPOSE

a first aid would care ointment

Keep out of reach of children

INDICATIONS AND USAGE

cleanse area to be treated, apply directly to the would, repeat 1 to 3 times daily as necessary

WARNINGS

for external use only, in case of deep puncture wounds, consult a veterinarian, if redness, irritation or swelling persists, discontinue us and consult a veterinarian

DOSAGE AND ADMINISTRATION

For external use only